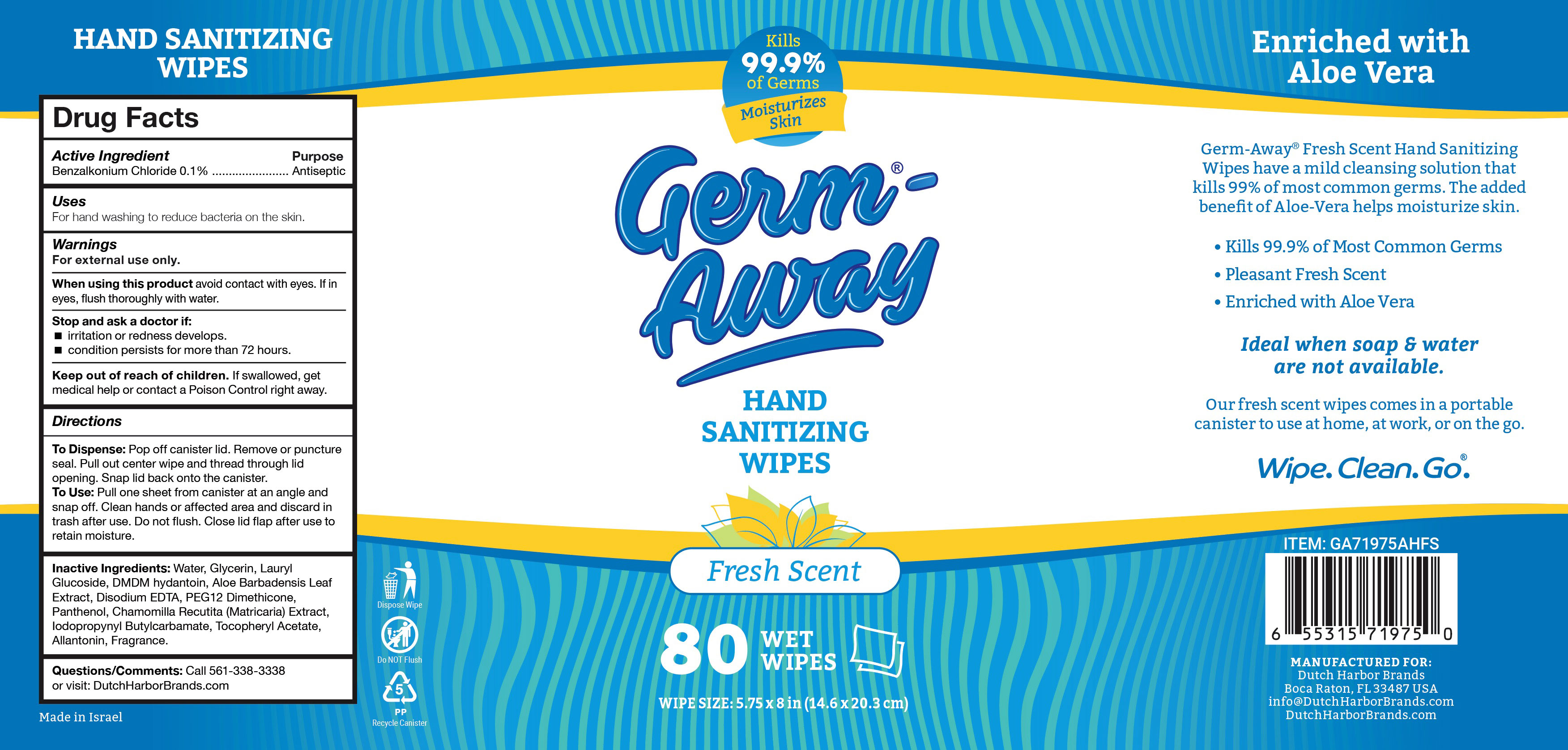 DRUG LABEL: Germ-Away
NDC: 74680-111 | Form: CLOTH
Manufacturer: Unico International Trading Corp
Category: otc | Type: HUMAN OTC DRUG LABEL
Date: 20260108

ACTIVE INGREDIENTS: BENZALKONIUM CHLORIDE 1 mg/1 g
INACTIVE INGREDIENTS: 2,2'-OXYDIPROPANOL; TETRAHYDROLINALOOL; 4-TERT-BUTYLCYCLOHEXYL ACETATE; ANHYDROUS CITRIC ACID; POTASSIUM SORBATE; SODIUM HYDROXYMETHYLGLYCINATE; PANTHENOL; DECYL GLUCOSIDE; ALOE VERA LEAF; WATER; CHAMOMILE; GLYCERIN; VIRIDIFLOROL; SODIUM BENZOATE; ALLANTOIN; PEG-12 DIMETHICONE (300 CST); .ALPHA.-TOCOPHEROL ACETATE; EDETATE SODIUM

Germ-Away

Active Ingredient

Benzalkonium Chloride 0.1%

Purpose

Anti-bacterial

Usage

Pull one sheet from canister at an angle. Sanitize hands or other affected area. Discard in trash after use. Do not flush. Close lid flap after use to retain moisture.

Dispensing instructions

Pop off canister lid. Remove or puncture seal. Pull out center wipe and thread through lid opening. Snap lid back onto the canister.

Inactive Ingredients

potassium sorbate, sodium hydroxymethylglycinate, aloe vera leaf, anhydrous citric acid, panthenol, water, decyl glucoside, chamomile, allantoin, peg-12 dimethicone, alpha-tocopherol acetate, edetate sodium, glycerin, sodium benzoate, fragrance

Keep out of the reach of children

Warnings

For external use only. Do not use in the eyes.

Keep out of eyes. In case of eye contact, rinse with water. If irritation develops, discontinue use. Consult doctor if irritation persists for more than 72 hours.

If swallowed, seek medical attention or contact a Poison Control Center.